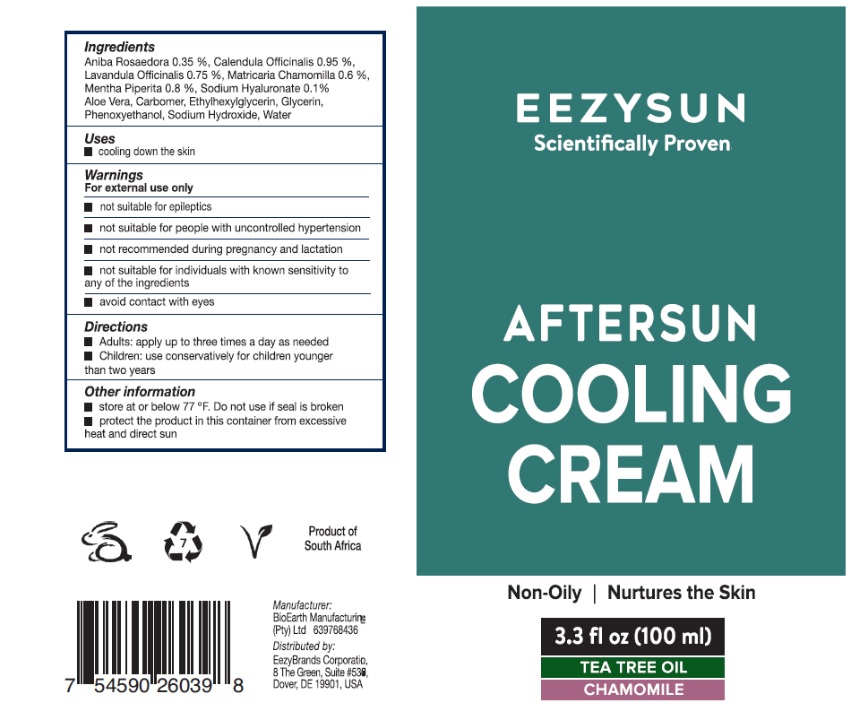 DRUG LABEL: Eezysun Aloe Vera After Sun
NDC: 70116-011 | Form: GEL
Manufacturer: BIO EARTH MANUFACTURING (PTY) LTD
Category: homeopathic | Type: HUMAN OTC DRUG LABEL
Date: 20241024

ACTIVE INGREDIENTS: ANIBA ROSAEODORA WHOLE 0.1 g/100 mL; CALENDULA OFFICINALIS FLOWERING TOP 0.1 g/100 mL; HYALURONIC ACID 0.5 g/100 mL; LAVANDULA ANGUSTIFOLIA SUBSP. ANGUSTIFOLIA FLOWER 0.3 g/100 mL; MATRICARIA CHAMOMILLA WHOLE 0.4 g/100 mL; MENTHA X PIPERITA WHOLE 0.15 g/100 mL
INACTIVE INGREDIENTS: ALOE VERA LEAF POLYSACCHARIDES; ROSEWOOD OIL; CARBOMER HOMOPOLYMER, UNSPECIFIED TYPE; ETHYLHEXYLGLYCERIN; GLYCERIN; PEPPERMINT OIL; PHENOXYETHANOL; HYALURONATE SODIUM; SODIUM HYDROXIDE; WATER

Active ingredients

Aniba Rosaedora 0.1%, Calendula Officinails 0.1% , Hyaluronic Acid 0.5%, Lavandula Officinalis 0.3%, Matricaria Chamomilla 0.4%, Mentha Piperita 0.15%

Purpose

Relaxing, cooling, anti-inflammatory, soothing, relieving

Uses

Cooling down the skin

Warnings

For external use only.

- Not suitable for epileptics
- Not suitable for people with uncontrolled hyper-tension.
- Not recommended during pregnancy and lactation
- Not suitable for individuals with known sensitivity to any of the ingredients.
- Avoid contact with eyes.

Directions

Adults: Apply up to three times per day as needed
Children: Use conservatively for children younger than two years

Inactive ingredients

Aloe Vera, Aniba Rosaedora, Carbomer, Ethylhexylglycerin, Glycerin, Mentha Piperita, Phenoxyethanol, Sodium Hyaluronate, Sodium Hydroxide, Water

Other information

- store at or below 77 F°. Do not use if seal is broken.
- product the product in this container from excessive heat and direact sun